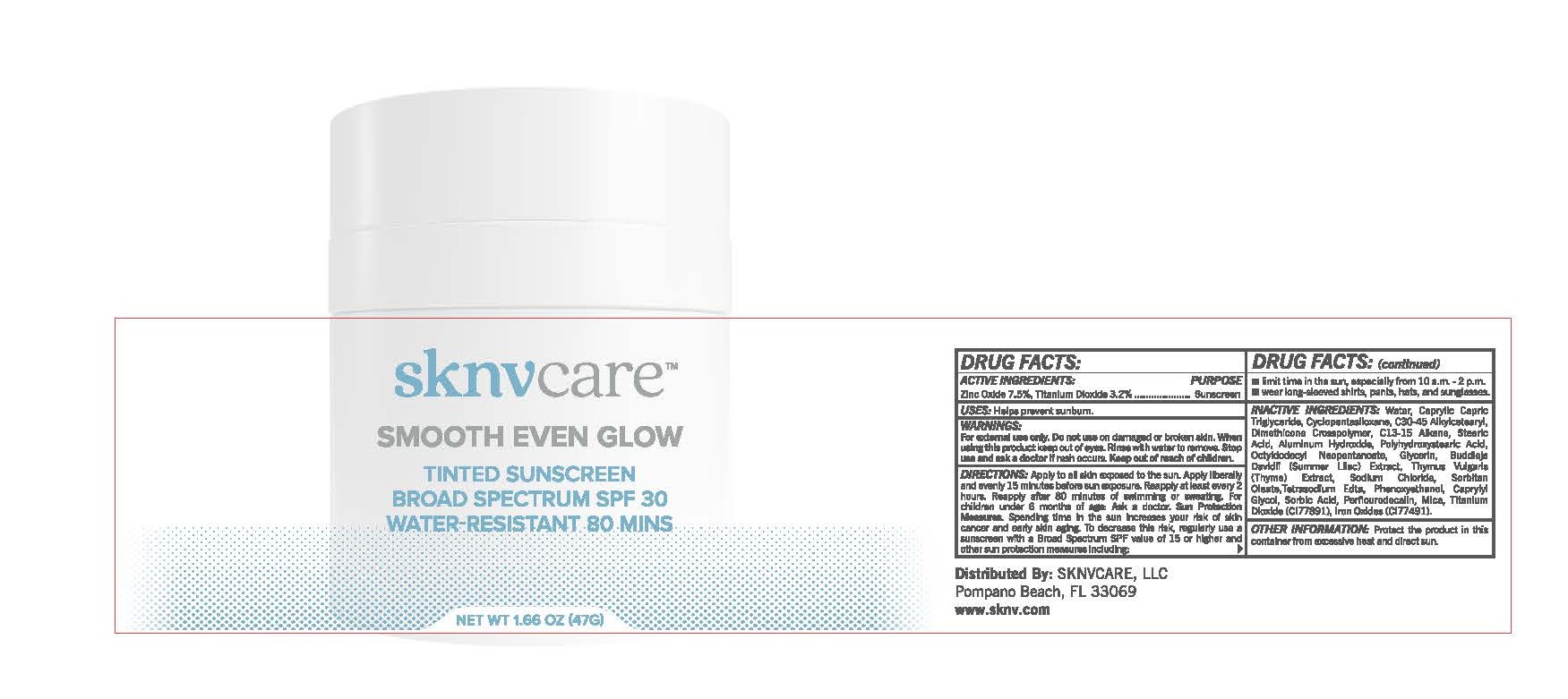 DRUG LABEL: Smooth Even Glow
NDC: 82704-0651 | Form: CREAM
Manufacturer: SKNVcare, LLC
Category: otc | Type: HUMAN OTC DRUG LABEL
Date: 20250925

ACTIVE INGREDIENTS: ZINC OXIDE 7.5 g/100 g; TITANIUM DIOXIDE 3.2 g/100 g
INACTIVE INGREDIENTS: POLYHYDROXYSTEARIC ACID (2300 MW); MICA; ALUMINUM HYDROXIDE; WATER; BUDDLEJA DAVIDII LEAF; THYMUS VULGARIS LEAF; CAPRYLIC/CAPRIC TRIGLYCERIDE; DIMETHICONE CROSSPOLYMER (450000 MPA.S AT 12% IN CYCLOPENTASILOXANE); C13-15 ALKANE; GLYCERIN; OCTYLDODECYL NEOPENTANOATE; PERFLUOROMETHYLDECALIN; PHENOXYETHANOL; CAPRYLYL GLYCOL; SORBIC ACID; SODIUM CHLORIDE; SORBITAN MONOOLEATE; TETRASODIUM EDTA; C30-45 ALKYL CETEARYL DIMETHICONE CROSSPOLYMER; STEARIC ACID; CYCLOPENTASILOXANE

Smooth Even Glow
Tinted Sunscreen
Broad Spectrum SPF 30
Water-Resistant 80 MINS

Drug Facts

Active Ingredients

Zinc Oxide 7.5%

Titanium Dioxide 3.2%

Purpose

Sunscreen

Uses

- helps prevent sunburn
- if used as directed with other sun protection measures (see Directions), decreases the risk of skin cancer and early skin aging caused by the sun

Warnings

For external use only

Do not useon damaged or broken skin

WHEN USING

When using this productkeep out of eyes. Rinse with water to remove.

Stop use and ask a doctorif rash occurs

Keep out of reach of children.If product is swallowed, get medical help or contact a Poison Control Center right away.

Directions

- apply liberally 15 minutes before sun exposure
- reapply:
  - after 80 minutes of swimming or sweating
  - immediately after towel drying
  - at least every 2 hours
- Sun Protection Measures. Spending time in the sun increases your risk of skin cancer and early skin aging. To decrease this risk, regularly use a sunscreen with a broad spectrum SPF 15 or higher and other sun protection measures including:
  - limit time in the sun, especially from 10 a.m. - 2 p.m.
  - wear long-sleeve shirts, pants, hats and sunglasses
- children under 6 months: Ask a doctor

Inactive Ingredients

Water, Caprylic Capric Triglyceride, Cyclopentasiloxane, C30-45 Alkylcetearyl, Dimethicone Crosspolymer, C13-15 Alkane, Stearic Acid, Aluminum Hydroxide, Polyhydroxystearic Acid, Octyldodecyl Neopentanoate, Glycerin, Buddleja Davidii (Summer Lilac) Extract, Thymus Vulgaris (Thyme) Extract, Sodium Chloride, Sorbitan Oleate,Tetrasodium Edta, Phenoxyethanol, Caprylyl Glycol, Sorbic Acid, Perflourodecalin, Mica, Titanium Dioxide (CI77891), Iron Oxides (CI77491).

Other Information

- protect this product from excessive heat and direct sun